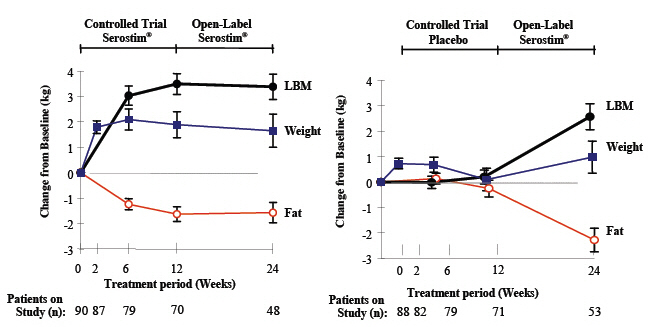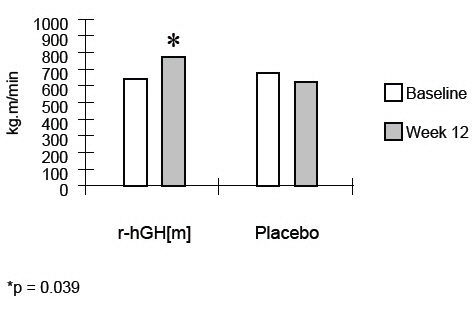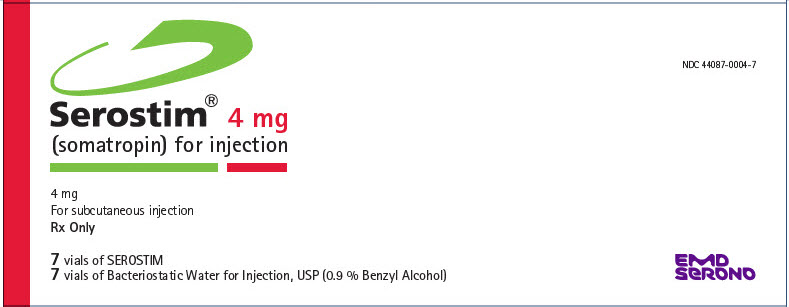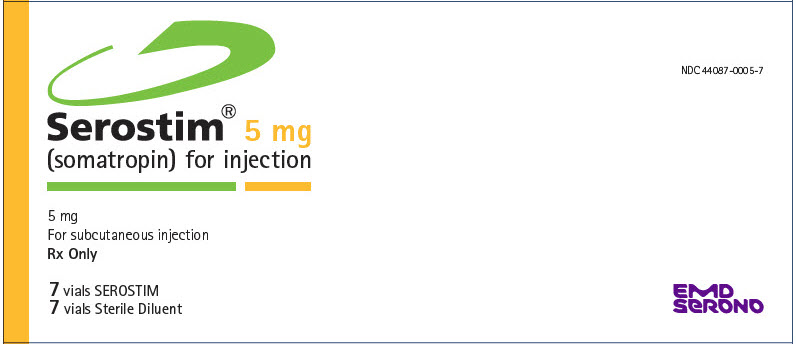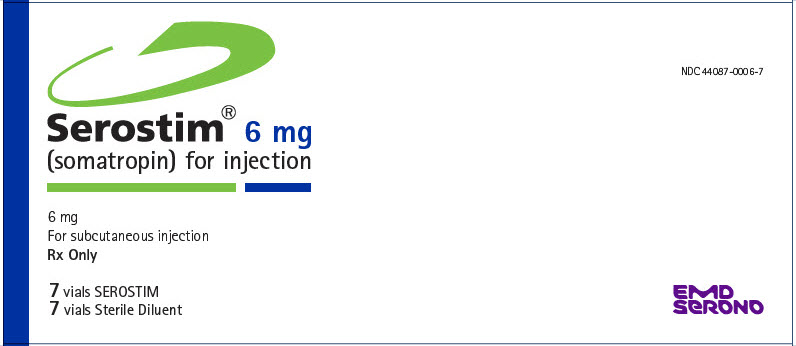 DRUG LABEL: Serostim
NDC: 44087-0004 | Form: KIT | Route: SUBCUTANEOUS
Manufacturer: EMD Serono, Inc.
Category: prescription | Type: HUMAN PRESCRIPTION DRUG LABEL
Date: 20220202

ACTIVE INGREDIENTS: SOMATROPIN 4 mg/1 mL
INACTIVE INGREDIENTS: SUCROSE 27.3  mg/1 mL; PHOSPHORIC ACID 0.9 mg/1 mL; WATER; BENZYL ALCOHOL

HIGHLIGHTS OF PRESCRIBING INFORMATION

These highlights do not include all the information needed to use SEROSTIM® safely and effectively. See full prescribing information for SEROSTIM.
SEROSTIM (somatropin) for injection, for subcutaneous use
Initial U.S. Approval: 1987

1 INDICATIONS AND USAGE

SEROSTIM is indicated for the treatment of HIV patients with wasting or cachexia to increase lean body mass and body weight, and improve physical endurance (1)

2 DOSAGE AND ADMINISTRATION

- The recommended dose of SEROSTIM is 0.1 mg/kg subcutaneously (SC) daily (up to 6 mg) at bedtime for HIV patients with wasting or cachexia (2.1)
- Injection sites, which may be located on thigh, upper arm, abdomen or buttock, should be rotated to avoid local irritation (2.2)

3 DOSAGE FORMS AND STRENGTHS

- Single-dose administration (to be administered with Sterile Water for Injection) (3):
  SEROSTIM 5 mg/ vial
  SEROSTIM 6 mg/ vial
- Multi-dose administration (to be administered with Bacteriostatic Water for Injection):
  SEROSTIM 4 mg/ vial

4 CONTRAINDICATIONS

- Acute Critical Illness (4)
- Active Malignancy (4)
- Diabetic Retinopathy (4)
- Hypersensitivity to somatropin or excipients (4)

5 WARNINGS AND PRECAUTIONS

- Acute Critical Illness: Increased mortality in patients with acute critical illness following open heart surgery, abdominal surgery or multiple accidental trauma, or those with acute respiratory failure has been reported after treatment with pharmacologic amounts of somatropin (5.1)
- Concomitant Antiretroviral Therapy: In vitro experimental systems have demonstrated the potential to potentiate HIV replication. No significant somatropin-associated increase in viral load was observed in clinical trials. HIV patients should be maintained on antiretroviral therapy for the duration of SEROSTIM treatment (5.2)
- Neoplasms: Monitor all patients with a history of any neoplasm routinely while on somatropin therapy for progression, recurrences, or development of a tumor (5.3)
- Impaired Glucose Tolerance/Diabetes: May be unmasked. Periodically monitor glucose levels. Dose adjustment of concurrent antihyperglycemic drugs in diabetics may be required (5.4)
- Intracranial Hypertension: Exclude preexisting papilledema. May develop and is usually reversible after discontinuation or dose reduction (5.5)
- Hypersensitivity: Serious hypersensitivity reactions may occur. In the event of an allergic reaction, seek prompt medical attention (5.6)
- Fluid Retention (edema, arthralgia)/Carpal Tunnel Syndrome: May occur frequently. Reduce dose as necessary (5.7)
- Pancreatitis: Consider pancreatitis in patients with persistent severe abdominal pain (5.9)

6 ADVERSE REACTIONS

Most common adverse reactions include (incidence >10%) tissue turgor (edema, myalgia, hypoesthesia) and musculoskeletal discomfort (arthralgia, pain in extremities) (6)

To report SUSPECTED ADVERSE REACTIONS, contact EMD Serono at 1-800-283-8088 ext 5563 or FDA at 1-800-FDA-1088 or www.fda.gov/medwatch

7 DRUG INTERACTIONS

- Inhibition of 11β-Hydroxysteroid Dehydrogenase Type 1: May require the initiation of glucocorticoid replacement therapy. Patients treated with glucocorticoid replacement for previously diagnosed hypoadrenalism may require an increase in their maintenance doses (7.1)
- Cytochrome P450-Metabolized Drugs: Monitor carefully if used with somatropin (7.2)
- Oral Estrogen: Larger doses of somatropin may be required in women (7.3)
- Insulin and/or Oral/Injectable Hypoglycemic Agents: May require adjustment (7.4)

FULL PRESCRIBING INFORMATION

1 INDICATIONS AND USAGE

SEROSTIM (somatropin) is indicated for the treatment of HIV patients with wasting or cachexia to increase lean body mass and body weight, and improve physical endurance. Concomitant antiretroviral therapy is necessary.

2 DOSAGE AND ADMINISTRATION

SEROSTIM is administered by subcutaneous injection.

SEROSTIM therapy should be carried out under the regular guidance of a physician who is experienced in the diagnosis and management of HIV infection.

2.1 HIV-associated wasting or cachexia

The usual starting dose of SEROSTIM is 0.1 mg/kg subcutaneously once daily (up to a total dose of 6 mg). SEROSTIM should be administered subcutaneously once daily at bedtime according to the following body weight-based dosage recommendations:

Weight Range | Dose
>55kg (>121 lb) | 6 mg [Based on an approximate daily dosage of 0.1 mg/kg.] SC daily
45-55 kg (99-121 lb) | 5 mg SC daily
35-45 kg (75-99 lb) | 4 mg SC daily
<35 kg (<75 lb) | 0.1 mg/kg SC daily

Treatment with SEROSTIM 0.1 mg/kg every other day was associated with fewer side effects, and resulted in a similar improvement in work output, as compared with SEROSTIM 0.1 mg/kg daily. Therefore, a starting dose of SEROSTIM 0.1 mg/kg every other day should be considered in patients at increased risk for adverse effects related to recombinant human growth hormone therapy (i.e., glucose intolerance). In general, dose reductions (i.e., reducing the total daily dose or the number of doses per week) should be considered for side effects potentially related to recombinant human growth hormone therapy.

Most of the effect of SEROSTIM on work output and lean body mass was apparent after 12 weeks of treatment. The effect was maintained during an additional 12 weeks of therapy. There are no safety or efficacy data available from controlled studies in which patients were treated with SEROSTIM continuously for more than 48 weeks. There are no safety or efficacy data available from trials in which patients with HIV wasting or cachexia were treated intermittently with SEROSTIM.

2.2 Preparation and Administration

Each vial of SEROSTIM 5 mg or 6 mg is reconstituted with 0.5 to 1 mL Sterile Water for Injection, USP.

Each vial of SEROSTIM 4 mg is reconstituted in 0.5 to 1 mL of Bacteriostatic Water for Injection, USP (0.9% Benzyl Alcohol preserved). For patients sensitive to Benzyl Alcohol, SEROSTIM may be reconstituted with Sterile Water for Injection, USP [see Pediatric Use (8.4)].

When SEROSTIM is reconstituted with Sterile Water for Injection, USP, the reconstituted solution should be used immediately and any unused portion should be discarded.

When SEROSTIM is reconstituted with Bacteriostatic Water for Injection, USP (0.9% Benzyl Alcohol preserved) the reconstituted solution may be refrigerated (2-8°C/36-46°F) for up to 14 days.

Approximately 10% mechanical loss can be associated with reconstitution and administration from multi-dose vials.

To reconstitute SEROSTIM, inject the diluent into the vial of SEROSTIM aiming the liquid against the glass vial wall. Swirl the vial with a GENTLE rotary motion until contents are dissolved completely. DO NOT SHAKE. Parenteral drug products should always be inspected visually for particulate matter and discoloration prior to administration, whenever solution and container permit. SEROSTIM MUST NOT BE INJECTED if the solution is cloudy or contains particulate matter. Use it only if it is clear and colorless.

SEROSTIM can be administered using (1) a standard sterile, disposable syringe and needle, (2) a compatible SEROSTIM needle-free injection device or (3) a compatible SEROSTIM needle injection device. For proper use, refer to the Instructions for Use provided with the administration device.

Injection sites, which may be located on the thigh, upper arm, abdomen or buttock, should be rotated to avoid local irritation.

3 DOSAGE FORMS AND STRENGTHS

Single-use administration (to be reconstituted with Sterile Water for Injection):

- SEROSTIM 5 mg per vial
- SEROSTIM 6 mg per vial

Multi-use administration (to be reconstituted with Bacteriostatic Water for Injection):

- SEROSTIM 4 mg per vial

4 CONTRAINDICATIONS

- Acute Critical Illness
  Growth hormone therapy should not be initiated in patients with acute critical illness due to complications following open heart or abdominal surgery, multiple accidental trauma or acute respiratory failure [see Warnings and Precautions (5.1)].
- Active Malignancy
  In general, somatropin is contraindicated in the presence of active malignancy. Any preexisting malignancy should be inactive and its treatment complete prior to instituting therapy with somatropin. Somatropin should be discontinued if there is evidence of recurrent activity [see Warnings and Precautions (5.3)].
- Hypersensitivity
  SEROSTIM is contraindicated in patients with a known hypersensitivity to somatropin or any of its excipients. Systemic hypersensitivity reactions have been reported with postmarketing use of somatropin products [see Warnings and Precautions (5.6)].
- Diabetic Retinopathy
  Somatropin is contraindicated in patients with active proliferative or severe non-proliferative diabetic retinopathy.

5 WARNINGS AND PRECAUTIONS

5.1 Acute Critical Illness

Increased mortality in patients with acute critical illness due to complications following open heart surgery, abdominal surgery or multiple accidental trauma, or those with acute respiratory failure has been reported after treatment with pharmacologic amounts of somatropin. Two placebo-controlled clinical trials in non-growth hormone deficient adult patients (n=522) with these conditions revealed a significant increase in mortality (42% vs. 19%) among somatropin-treated patients (doses 5.3-8 mg/day) compared to those receiving placebo [see Contraindications (4)].

5.2 Concomitant Antiretroviral Therapy

In some experimental systems, somatropin has been shown to potentiate HIV replication in vitro at concentrations ranging from 50-250 ng/mL. There was no increase in virus production when the antiretroviral agents, zidovudine, didanosine or lamivudine were added to the culture medium. Additional in vitro studies have shown that somatropin does not interfere with the antiviral activity of zalcitabine or stavudine. In the controlled clinical trials, no significant somatropin-associated increase in viral burden was observed. However, the protocol required all participants to be on concomitant antiretroviral therapy for the duration of the study. In view of the potential for acceleration of virus replication, it is recommended that HIV patients be maintained on antiretroviral therapy for the duration of SEROSTIM treatment.

5.3 Neoplasms

Because malignancies are more common in HIV positive individuals, the risks and benefits of starting somatropin in HIV positive patients should be carefully considered before initiating SEROSTIM treatment and patients should be monitored carefully for the development of neoplasms if treatment with somatropin is initiated.

Monitor all patients with a history of any neoplasm routinely while on somatropin therapy for progression or recurrence of the tumor [see Contraindications (4)].

Monitor patients on somatropin therapy carefully for increased growth, or potential malignant changes of preexisting nevi.

5.4 Impaired Glucose Tolerance/Diabetes

Hyperglycemia may occur in HIV infected individuals due to a variety of reasons. In wasting patients, treatment with SEROSTIM 0.1 mg/kg daily and 0.1 mg/kg every other day for 12 weeks was associated with approximately 10 mg/dL and 6 mg/dL increases in mean fasting blood glucose concentrations, respectively. The increases occurred early in treatment. Patients with other risk factors for glucose intolerance should be monitored closely during SEROSTIM therapy.

During safety surveillance of patients with HIV-associated wasting, cases of new onset impaired glucose tolerance, new onset type 2 diabetes mellitus and exacerbation of preexisting diabetes mellitus have been reported in patients receiving SEROSTIM. Some patients developed diabetic ketoacidosis and diabetic coma. In some patients, these conditions improved when SEROSTIM was discontinued, while in others, the glucose intolerance persisted. Some of these patients required initiation or adjustment of antidiabetic treatment while on SEROSTIM.

In clinical trials of SEROSTIM conducted in HIV patients with lipodystrophy (an unapproved indication), evidence of dose-dependent glucose intolerance and related adverse reaction was observed at doses of 4 mg SEROSTIM daily and 4 mg SEROSTIM every other day for 12 weeks [see Adverse Reactions (6.1)].

5.5 Intracranial Hypertension

Intracranial hypertension (IH) with papilledema, visual changes, headache, nausea, and/or vomiting has been reported in a small number of patients treated with somatropin products. Symptoms usually occurred within the first eight (8) weeks after the initiation of somatropin therapy. In all reported cases, IH-associated signs and symptoms rapidly resolved after cessation of therapy or a reduction of the somatropin dose. Funduscopic examination should be performed routinely before initiating treatment with somatropin to exclude preexisting papilledema, and periodically during the course of somatropin therapy. If papilledema is observed by funduscopy during somatropin treatment, treatment should be stopped. If somatropin-induced IH is diagnosed, treatment with somatropin can be restarted at a lower dose after IH-associated signs and symptoms have resolved.

5.6 Severe Hypersensitivity

Serious systemic hypersensitivity reactions including anaphylactic reactions and angioedema have been reported with postmarketing use of somatropin products. Patients and caregivers should be informed that such reactions are possible and that prompt medical attention should be sought if an allergic reaction occurs [see Contraindications (4)].

5.7 Fluid Retention/Carpal Tunnel Syndrome

Increased tissue turgor (swelling, particularly in the hands and feet) and musculoskeletal discomfort (pain, swelling and/or stiffness) may occur during treatment with SEROSTIM, but may resolve spontaneously, with analgesic therapy, or after reducing the frequency of dosing [see Dosage and Administration (2.1)].

Carpal tunnel syndrome may occur during treatment with SEROSTIM. If the symptoms of carpal tunnel syndrome do not resolve by decreasing the weekly number of doses of SEROSTIM, it is recommended that treatment be discontinued.

5.8 Lipoatrophy

When somatropin is administered subcutaneously at the same site over a long period of time, tissue atrophy may result. This can be avoided by rotating the injection site [see Dosage and Administration (2.2)].

5.9 Pancreatitis

Cases of pancreatitis have been reported rarely in children and adults receiving somatropin treatment, with some evidence supporting a greater risk in children compared with adults. Published literature indicates that girls who have Turner syndrome may be at greater risk than other somatropin-treated children. Pancreatitis should be considered in any somatropin-treated patient, especially a child who develops abdominal pain.

6 ADVERSE REACTIONS

The following important adverse reactions are also described elsewhere in the labeling:

Acute Critical Illness [see Warnings and Precautions (5.1)]

Neoplasms [see Warnings and Precautions (5.3)]

Impaired glucose tolerance and diabetes mellitus [see Warnings and Precautions (5.4)]

Intracranial hypertension [see Warnings and Precautions (5.5)]

Severe hypersensitivity [see Warnings and Precautions (5.6)]

Fluid retention/Carpal tunnel syndrome [see Warnings and Precautions (5.7)]

Lipoatrophy [see Warnings and Precautions (5.8)]

Pancreatitis [see Warnings and Precautions (5.9)]

6.1 Clinical Trials Experience

Because clinical trials are conducted under widely varying conditions, adverse reaction rates observed in the clinical trials of a drug cannot be directly compared to rates in the clinical trials of another drug and may not reflect the rates observed in clinical practice.

Clinical trials in HIV-associated wasting or cachexia:

In the 12-week, placebo-controlled Clinical Trial 2, 510 patients were treated with SEROSTIM. The most common adverse reactions judged to be associated with SEROSTIM were musculoskeletal discomfort and increased tissue turgor (swelling, particularly of the hands or feet), and were more frequently observed when SEROSTIM 0.1 mg/kg was administered on a daily basis [Table 1 and Warnings and Precautions (5)]. These symptoms often subsided with continued treatment or dose reduction. Approximately 23% of patients receiving SEROSTIM 0.1 mg/kg daily and 11% of patients receiving 0.1 mg/kg every other day required dose reductions. Discontinuations as a result of adverse reactions occurred in 10.3% of patients receiving SEROSTIM 0.1 mg/kg daily and 6.6% of patients receiving 0.1 mg/kg every other day. The most common reasons for dose reduction and/or drug discontinuation were arthralgia, myalgia, edema, carpal tunnel syndrome, elevated glucose levels, and elevated triglyceride levels.

Clinical adverse reactions which occurred during the first 12 weeks of study in at least 5% of the patients in either active treatment group and at an incidence greater than placebo are listed below, without regard to causality assessment.

Table 1: Controlled Clinical Trial 2 Adverse Reactions Occurring in at least 5% of Patients in one of the Treatment Groups, and at an Incidence Greater than Placebo
 | Placebo | 0.1 mg/kg every other day SEROSTIM | 0.1 mg/kg daily SEROSTIM
 | Patients (n=247) | Patients (n=257) | Patients (n=253)
Body System Preferred Term | % | % | %
Musculoskeletal System Disorders
Arthralgia | 11.3 | 24.5 | 36.4
Myalgia | 11.7 | 17.9 | 30.4
Arthrosis | 3.6 | 7.8 | 10.7
Gastrointestinal System Disorders
Nausea | 4.9 | 5.4 | 9.1
Body As A Whole - General Disorders
Edema Peripheral | 2.8 | 11.3 | 26.1
Fatigue | 4.5 | 3.5 | 5.1
Endocrine Disorders
Gynecomastia | 0.4 | 3.5 | 5.5
Central and Peripheral Nervous System Disorders
Paresthesia | 4.5 | 7.4 | 7.9
Hypoesthesia | 2.4 | 1.6 | 5.1
Metabolic and Nutritional Disorders
Edema Generalized | 1.2 | 1.2 | 5.9

Adverse reactions that occurred in 1% to less than 5% of trial participants receiving SEROSTIM during the first 12 weeks of Clinical Trial 2 thought to be related to SEROSTIM included dose dependent edema, periorbital edema, carpal tunnel syndrome, hyperglycemia and hypertriglyceridemia.

During the 12-week, placebo-controlled portion of Clinical Trial 2, the incidence of hyperglycemia reported as an adverse reaction was 3.6% for the placebo group, 1.9% for the 0.1 mg/kg every other day group and 3.2% for the 0.1 mg/kg daily group. One case of diabetes mellitus was noted in the 0.1 mg/kg daily group during the first 12-weeks of therapy. In addition, during the extension phase of Clinical Trial 2, two patients converted from placebo to full dose SEROSTIM, and 1 patient converted from placebo to half-dose SEROSTIM, were discontinued because of the development of diabetes mellitus.

The types and incidences of adverse reactions reported during the Clinical Trial 2 extension phase were not different from, or greater in frequency than those observed during the 12-week, placebo-controlled portion of Clinical Trial 2.

Adverse reactions from treatment with SEROSTIM in clinical trials in HIV lipodystrophy

SEROSTIM was evaluated for the treatment of patients with HIV lipodystrophy in two double-blind, placebo-controlled trials that excluded patients with a history of diabetes, impaired fasting glucose or impaired glucose (approximately 20% of the patients screened were excluded from study enrollment as a result of a diagnosis of diabetes or glucose intolerance). The studies included a 12-week double-blind, placebo-controlled, parallel group "induction" phase followed by maintenance phases of different durations (12 and 24 weeks, respectively). In the initial 12-week treatment periods of the two, placebo-controlled clinical trials, 406 patients were treated with SEROSTIM. Clinical adverse reactions which occurred during the first 12 weeks of both studies combined in at least 5% of the patients in either of the two active treatment groups are listed by treatment group in Table 2, without regard to causality assessment. The most common adverse reactions judged to be associated with SEROSTIM were edema, arthralgia, pain in extremity, hypoesthesia, myalgia, and blood glucose increased, all of which were more frequently observed when SEROSTIM 4 mg was administered on a daily basis compared with alternate days. These symptoms often subsided with dose reduction. During the 12-week induction phase, 1) approximately 26% of patients receiving SEROSTIM 4 mg daily and 19% of patients receiving SEROSTIM4 mg every other day required dose reductions; and 2) discontinuations as a result of adverse reactions occurred in 13% of patients receiving SEROSTIM 4 mg daily and 5% of patients receiving SEROSTIM 4 mg every other day. The most common reasons for dose reduction and/or drug discontinuation were peripheral edema, hyperglycemia (including blood glucose increased, blood glucose abnormal, and hyperglycemia), and arthralgia.

Table 2: Controlled HIV Lipodystrophy Studies 1 and 2 Combined –Adverse Reactions with >5% Incidence in Either Active Treatment Arm
 | Placebo | SEROSTIM 4 mg every other day [Study 22388 only] | SEROSTIM 4 mg daily
 | Patients (n=159) | Patients (n=80) | Patients (n=326)
System Organ Class Preferred Term | % | % | %
Musculoskeletal and connective tissue disorders
Arthralgia | 11.9 | 27.8 | 37.1
Pain in extremity | 3.8 | 5.0 | 19.3
Myalgia | 3.8 | 2.5 | 12.6
Musculoskeletal stiffness | 1.9 | 3.8 | 8.0
Joint stiffness | 1.3 | 3.8 | 7.7
Joint swelling | 0.6 | 5.0 | 6.1
General disorders and administration site conditions
Edema peripheral | 3.8 | 18.8 | 45.4
Fatigue | 1.9 | 6.3 | 8.9
Nervous system disorders
Hypoesthesia | 0.6 | 8.8 | 15.0
Paraesthesia | 2.5 | 12.5 | 11.0
Investigations (Laboratory Evaluations)
Blood glucose increased [similar terms were grouped together and reported below] | 2.5 | 3.8 | 13.8
Metabolism and nutrition disorders
Hyperglycemia | 0.6 | 8.8 | 7.1
Fluid retention | 0.6 | 2.5 | 5.2
Gastrointestinal disorders
Nausea | 2.5 | 1.3 | 6.1

Glucose metabolism related adverse reactions: During the initial 12-week treatment periods of Studies 1 and 2, the incidence of glucose-related adverse reactions was 4% for the placebo group, 13% for the 4 mg every other day group and 22% for the 4 mg daily group.

Twenty-three patients discontinued due to hyperglycemia while receiving SEROSTIM during any phase of these studies (3.2% in the 12-week induction phases and 2.1% in the extension phases).

Breast-Related Terms: When grouped together, breast-related adverse reactions (e.g. nipple pain, gynecomastia, breast pain/mass/tenderness/swelling/edema/hypertrophy) had an incidence of 1% for the placebo group, 3% for the SEROSTIM 4 mg every other day group and 6% for the SEROSTIM 4 mg daily group.

Adverse reactions that occurred in 1% to less than 5% of trial participants receiving SEROSTIM during the first 12 weeks of HIV Lipodystrophy Studies 1 and 2 thought to be related to SEROSTIM include carpal tunnel syndrome, Tinel's sign and facial edema.

The adverse reactions reported for SEROSTIM 4 mg every other day during the maintenance phase of HIV Lipodystrophy Study 1 (Week 12 to Week 24) were similar in frequency and quality to those observed after treatment with SEROSTIM 4 mg every other day during the 12-week induction phase.

IGF-1 serum concentrations increased statistically in SEROSTIM-treated patients when compared to placebo (Table 3). In the SEROSTIM treated patients at baseline, the proportion of subjects with serum IGF-1 SDS levels ≥ +2 was approximately 10 to 20%, while with treatment with either dose regimen of SEROSTIM the percentage increased to 80 to 90% by Week 12.

Table 3: Change from Baseline to Week 12 in Serum IGF-1 SDS After Treatment with SEROSTIM 4 mg daily vs. Placebo (Modified ITT Population; Studies 1 and 2 Combined)
 |  | Placebo | SEROSTIM 4 mg every other day | SEROSTIM 4 mg daily
Time Point | Statistic | (n=145) | (n=79) | (n=290)
Baseline | Mean (SD) Range | 0.4 (1.4) (-2.5, 4.8) | 1.3 (2.1) (-2.0, 13.7) | 0.0 (1.6) (-3.0, 11.9)
Week 12 | Mean (SD) Range | 0.8 (1.6) (-2.6, 6.7) | 5.1 (3.4) (-0.7, 17.2) | 6.1 (5.0) (-1.8, 29.2)
Change from Baseline to | Mean (SD) Range | 0.4 (1.3) (-2.9, 7.7) | 3.9 (3.1) (-9.4, 11.8) | 6.1 (4.6) (-2.4, 24.3)
Week 12 | p-value [P-value from a Wilcoxon Signed Rank test on the change from baseline to Week 12.] | <0.001 | <0.001 | <0.001
 | Mean [Proportionally weighted least squares means from a two-way ANOVA model on raw data including effects for treatment, sex, and the treatment by sex interaction.] diff (SEM) |  | 3.5 (0.5) | 5.7 (0.4)
 | p-value [P-value from a two-way ANOVA model on ranked data including effects for treatment, sex, and the treatment by sex interaction.] |  | <0.001 | <0.001

As with all therapeutic proteins, there is potential for immunogenicity. The detection of antibody formation is highly dependent on the sensitivity and specificity of the assay. Additionally, the observed incidence of antibody (including neutralizing antibody) positivity in an assay may be influences by several factors including assay methodology, sample handling, timing of sample collection, concomitant medications, and underlying disease. For these reasons, comparison of the incidence of antibodies to SEROSTIM with the incidence of antibodies to other products may be misleading.

After 12 weeks of treatment, none of the 651 study participants with HIV-associated wasting treated with SEROSTIM for the first time developed detectable antibodies to growth hormone (> 4 pg binding). Patients were not rechallenged. Data beyond 3 months is not available.

6.2 Post-Marketing Experience

The following adverse reactions have been identified during post approval use of SEROSTIM. Because these reactions are reported voluntarily from a population of uncertain size, it is not always possible to reliably estimate their frequency or establish a causal relationship to drug exposure.

Hypersensitivity: Serious systemic hypersensitivity reactions including anaphylactic reactions and angioedema have been reported with postmarketing use of somatropin products [see Warnings and Precautions (5.6)].

Endocrine:

- new onset impaired glucose tolerance
- new onset type 2 diabetes mellitus
- exacerbation of preexisting diabetes mellitus
- diabetic ketoacidosis
- diabetic coma

In some patients, these conditions improved when SEROSTIM was discontinued, while in others the glucose intolerance persisted. Some of these patients required initiation or adjustment of antidiabetic treatment while on SEROSTIM [see Warnings and Precautions (5.4)].

Gastrointestinal: Pancreatitis [see Warnings and Precautions (5.9)].

7 DRUG INTERACTIONS

Formal drug interaction studies have not been conducted. No data are available on drug interactions between SEROSTIM and HIV protease inhibitors or the non-nucleoside reverse transcriptase inhibitors.

7.1 11β-Hydroxysteroid Dehydrogenase Type 1

The microsomal enzyme 11β-hydroxysteroid dehydrogenase type 1 (11βHSD-1) is required for conversion of cortisone to its active metabolite, cortisol, in hepatic and adipose tissue. Somatropin inhibits 11βHSD-1. Patients treated with glucocorticoid replacement for previously diagnosed hypoadrenalism may require an increase in their maintenance or stress doses following initiation of somatropin treatment; this may be especially true for patients treated with cortisone acetate and prednisone since conversion of these drugs to their biologically active metabolites is dependent on the activity of 11βHSD-1.

7.2 Cytochrome P450-metabolized drugs

Limited published data indicate that somatropin treatment increases cytochrome P450 (CYP450)-mediated antipyrine clearance in man. These data suggest that somatropin administration may alter the clearance of compounds metabolized by CYP450 liver enzymes (e.g., corticosteroids, sex steroids, anticonvulsants, cyclosporine). Therefore, careful monitoring is advised when somatropin is administered in combination with drugs metabolized by CYP450 liver enzymes. However, formal drug interaction studies have not been conducted.

7.3 Oral Estrogen

Because oral estrogens may reduce the serum IGF-1 response to somatropin treatment, girls and women receiving oral estrogen replacement may require greater somatropin dosages [see Dosage and Administration (2)].

7.4 Insulin and/or Other Oral/Injectable Hypoglycemic Agents

Patients with diabetes mellitus who receive concomitant treatment with somatropin may require adjustment of their doses of insulin and/or other hypoglycemic agents [see Warnings and Precautions (5.4)].

8 USE IN SPECIFIC POPULATIONS

8.1 Pregnancy

Reproduction studies have been performed in rats and rabbits. Doses up to 5 to 10 times the human dose, based on body surface area, have revealed no evidence of impaired fertility or harm to the fetus due to SEROSTIM. There are, however, no adequate and well-controlled studies in pregnant women. Because animal reproduction studies are not always predictive of human response, SEROSTIM should be used during pregnancy only if clearly needed.

8.3 Nursing Women

It is not known whether SEROSTIM is excreted in human milk. Because many drugs are excreted in human milk, caution should be exercised when SEROSTIM is administered to a nursing woman.

8.4 Pediatric Use

Safety and effectiveness in pediatric patients with HIV have not been established. Available evidence suggests that somatropin clearance is similar in adults and children, but no pharmacokinetic studies have been conducted in children with HIV.

In two small studies, 11 children with HIV-associated failure to thrive were treated subcutaneously with human growth hormone. In one study, five children (age range, 6 to 17 years) were treated with 0.04 mg/kg/day for 26 weeks. In a second study, six children (age range, 8 to 14 years) were treated with 0.07 mg/kg/day for 4 weeks. Treatment appeared to be well tolerated in both studies. The preliminary data collected on a limited number of patients with HIV-associated failure to thrive appear to be consistent with safety observations in growth hormone-treated adults with HIV wasting.

Benzyl alcohol, a component of this product, has been associated with serious adverse events and death, particularly in pediatric patients. The "gasping syndrome," (characterized by central nervous system depression, metabolic acidosis, gasping respirations, and high levels of benzyl alcohol and its metabolites found in the blood and urine) has been associated with benzyl alcohol dosages >99 mg/kg/day in neonates and low-birth weight neonates. Additional symptoms may include gradual neurological deterioration, seizures, intracranial hemorrhage, hematologic abnormalities, skin breakdown, hepatic and renal failure, hypotension, bradycardia, and cardiovascular collapse. Practitioners administering this and other medications containing benzyl alcohol should consider the combined daily metabolic load of benzyl alcohol from all sources.

8.5 Geriatric Use

Clinical studies with SEROSTIM did not include sufficient numbers of subjects aged 65 and over to determine whether they respond differently from younger subjects. Elderly patients may be more sensitive to the action of somatropin, and therefore, may be more prone to develop adverse reactions. A lower starting dose and smaller dose increments should be considered for older patients [see Dosage and Administration (2)].

8.6 Hepatic Impairment

No studies have been conducted for SEROSTIM in patients with hepatic impairment [see Clinical Pharmacology (12.3)].

8.7 Renal Impairment

Subjects with chronic renal failure tend to have decreased somatropin clearance compared to those with normal renal function. However, no studies have been conducted for SEROSTIM in patients with renal impairment [see Clinical Pharmacology (12.3)].

8.8 Gender Effect

Biomedical literature indicates that a gender-related difference in the mean clearance of r-hGH could exist (clearance of r-hGH in males > clearance of r-hGH in females). However, no gender-based analysis is available for SEROSTIM in normal volunteers or patients infected with HIV.

10 OVERDOSAGE

Short-Term

Acute overdosage could lead initially to hypoglycemia and subsequently to hyperglycemia.

Long-Term

Long-term overdosage could result in signs and symptoms of acromegaly consistent with the known effects of excess growth hormone.

11 DESCRIPTION

SEROSTIM is a human growth hormone (hGH) produced by recombinant DNA technology. SEROSTIM has 191 amino acid residues and a molecular weight of 22,125 daltons. Its amino acid sequence and structure are identical to the dominant form of human pituitary growth hormone. SEROSTIM is produced by a mammalian cell line (mouse C127) that has been modified by the addition of the hGH gene. SEROSTIM is secreted directly through the cell membrane into the cell-culture medium for collection and purification.

SEROSTIM is a sterile lyophilized powder intended for subcutaneous injection after reconstitution to its liquid form.

Vials of SEROSTIM contain either 4 mg, 5 mg, or 6 mg. Each vial contains the following:

 | Vials
 | 4 mg | 5 mg | 6 mg
Component
Somatropin | 4 mg | 5 mg | 6 mg
Sucrose | 27.3 mg | 34.2 mg | 41 mg
Phosphoric acid | 0.9 mg | 1.2 mg | 1.4 mg

Each 4 mg multi-vial is supplied in a combination package with Bacteriostatic Water for Injection, USP (0.9% Benzyl Alcohol). The pH is adjusted with sodium hydroxide of phosphoric acid to give a pH of 7.4 to 8.5 after reconstitution.

Each 5 mg single-use vial is supplied in a combination package with Sterile Water for Injection, USP. The pH is adjusted with sodium hydroxide or phosphoric acid to give a pH of 6.5 to 8.5 after reconstitution.

Each 6 mg single-use vial is supplied in a combination package with Sterile Water for Injection, USP. The pH is adjusted with sodium hydroxide of phosphoric acid to give a pH of 7.4 to 8.5 after reconstitution.

12 CLINICAL PHARMACOLOGY

12.1 Mechanism of Action

SEROSTIM is an anabolic and anticatabolic agent which exerts its influence by interacting with specific receptors on a variety of cell types including myocytes, hepatocytes, adipocytes, lymphocytes, and hematopoietic cells. Some, but not all of its effects, are mediated by insulin-like growth factor-1 (IGF-1).

12.2 Pharmacodynamics

Effects on Protein, Lipid and Carbohydrate Metabolism

A one-week study in 6 patients with HIV-associated wasting has shown that treatment with SEROSTIM 0.1 mg/kg/day improved nitrogen balance, increased protein-sparing lipid oxidation, and had little effect on overall carbohydrate metabolism.

Decreases in trunk fat and total body fat, and increases in lean body mass were observed during two double-blind, placebo-controlled studies wherein SEROSTIM vs. placebo were administered daily for 12 weeks to patients with HIV Lipodystrophy [see Clinical Studies (14)].

Effects on Nitrogen and Mineral Retention

In the one-week study in 6 patients with HIV-associated wasting, treatment with SEROSTIM resulted in the retention of phosphorous, potassium, nitrogen, and sodium. The ratio of retained potassium and nitrogen during SEROSTIM therapy was consistent with retention of these elements in lean tissue.

Physical Performance

Cycle ergometry work output and treadmill performance were examined in separate 12-week, placebo-controlled trials [see Clinical Studies (14)]. In both studies, work output improved significantly in the group receiving SEROSTIM 0.1 mg/kg/day subcutaneously vs placebo. Isometric muscle performance, as measured by grip strength dynamometry, declined, probably as a result of a transient increase in tissue turgor known to occur with SEROSTIM therapy.

12.3 Pharmacokinetics

Absorption: The absolute bioavailability after subcutaneous administration was determined to be 70 to 90%. The mean t½ after subcutaneous administration is significantly longer than that seen after intravenous administration in normal male volunteers down-regulated with somatostatin (approximately 4.0 hrs. vs. 0.6 hrs.), indicating that the subcutaneous absorption of somatropin is a rate-limiting process.

Distribution: The steady-state volume of distribution (Mean ± SD) following intravenous administration of somatropin in normal male volunteers is 12.0 ± 1.08 L.

Metabolism: Although the liver plays a role in the metabolism of GH, GH is primarily cleaved in the kidney. GH undergoes glomerular filtration and, after cleavage within the renal cells, the peptides and amino acids are returned to the systemic circulation.

Elimination: The t½ in nine patients with HIV-associated wasting with an average weight of 56.7 ± 6.8 kg, given a fixed dose of 6.0 mg somatropin subcutaneously was 4.28 ± 2.15 hrs, similar to that observed in normal male volunteers. The renal clearance of r-hGH after subcutaneous administration in nine patients with HIV-associated wasting was 0.0015 ± 0.0037 L/h. No significant accumulation of r-hGH appears to occur after 6 weeks of daily dosing as indicated.

Specific Populations:

Pediatric: Available evidence suggests that r-hGH clearances are similar in adults and children, but no pharmacokinetic studies have been conducted in children with HIV.

Gender: Biomedical literature indicates that a gender-related difference in the mean clearance of r-hGH could exist (clearance of r-hGH in males > clearance of r-hGH in females). However, no gender-based analysis is available in normal volunteers or patients infected with HIV.

Race: No studies have been conducted to determine the effect of race on the pharmacokinetics of SEROSTIM.

Renal Impairment: Subjects with chronic renal failure tend to have decreased somatropin clearance compared to those with normal renal function. However, no studies have been conducted to determine the effect of renal impairment on the pharmacokinetics of SEROSTIM.

Hepatic Impairment: No studies have been conducted to determine the effect of hepatic impairment on the pharmacokinetic of SEROSTIM.

13 NONCLINICAL TOXICOLOGY

13.1 Carcinogenesis, Mutagenesis, Impairment of Fertility

Long-term animal studies for carcinogenicity have not been performed with SEROSTIM. There is no evidence from animal studies to date of SEROSTIM-induced mutagenicity or impairment of fertility.

14 CLINICAL STUDIES

HIV-Associated Wasting or Cachexia

The clinical efficacy of SEROSTIM in HIV-associated wasting or cachexia was assessed in two placebo-controlled trials. All study subjects received concomitant antiretroviral therapy. There was no increase in the incidence of Kaposi's sarcoma (KS), lymphoma, or in the progression of cutaneous Kaposi's sarcoma in clinical studies of SEROSTIM. Patients with internal KS lesions were excluded from the studies. Potential effects on other malignancies are unknown.

Clinical Trial 1:

A 12-week, randomized, double-blind, placebo-controlled study followed by an open-label extension phase enrolled 178 patients with severe HIV wasting taking nucleoside analogue therapy (pre-HAART era). The primary endpoint was body weight. Body composition was assessed using dual energy X-ray absorptiometry (DXA) and physical function was assessed by treadmill exercise testing. Patients meeting the inclusion/exclusion criteria were treated with either placebo or SEROSTIM 0.1 mg/kg daily. Ninety-six percent (96%) were male. The average baseline CD4 count/microliter was 85. The results from one hundred forty (140) evaluable patients were analyzed (those completing the 12-week course of treatment and who were at least 80% compliant with study drug). After 12 weeks of therapy, the mean difference in weight increase between the SEROSTIM-treated group and the placebo-treated group was 1.6 kg (3.5 lb). Mean difference in lean body mass (LBM) change between the SEROSTIM-treated group and the placebo-treated group was 3.1 kg (6.8 lbs) as measured by DXA. Mean increase in weight and LBM, and mean decrease in body fat, were significantly greater in the SEROSTIM-treated group than in the placebo group (p=0.011, p<0.001, p<0.001, respectively) after 12 weeks of treatment (Figure 1). There were no significant changes with continued treatment beyond 12 weeks suggesting that the original gains of weight and LBM were maintained (Figure 1).

Treatment with SEROSTIM resulted in a significant increase in physical function as assessed by treadmill exercise testing. The median treadmill work output increased by 13% (p=0.039) at 12 weeks in the group receiving SEROSTIM (Figure 2). There was no improvement in the placebo-treated group at 12 weeks. Changes in treadmill performance were significantly correlated with changes in LBM.

Figure 1: Mean Changes in Body Composition

Figure 2: Median Treadmill Work Output

Clinical Trial 2:

A 12-week, randomized, double-blind, placebo-controlled study enrolled 757 patients with HIV-associated wasting, or cachexia. The primary efficacy endpoint was physical function as measured by cycle ergometry work output. Body composition was assessed using bioelectrical impedance spectroscopy (BIS) and also by dual energy X-ray absorptiometry (DXA) at a subset of centers. Patients meeting the inclusion/exclusion criteria were treated with either placebo, approximately 0.1 mg/kg every other day (qod) of SEROSTIM, or approximately 0.1 mg/kg daily at bedtime of SEROSTIM. All results were analyzed in intent-to-treat populations (for cycle ergometry work output, n=670). Ninety-one percent (91%) were male and 88% were on HAART anti-retroviral therapy. The average baseline CD4 count/µL was 446. Six hundred forty-six patients (646) completed the 12-week study and continued in the SEROSTIM treatment extension phase of the trial.

Clinical Trial 2 results are summarized in Tables 4 and 5:

Table 4: Mean (Median) of Cycle Work Output (kJ) Response after 12 weeks of Treatment ITT Population
 | Placebo | Half-Dose SEROSTIM [approximately 0.1 mg/kg every other day] | Full-Dose SEROSTIM [approximately 0.1 mg/kg daily]
Cycle work output (kJ) | n=222 | n=230 | n=218
Baseline | 25.92 (25.05) | 27.79 (26.65) | 27.57 (26.30)
Change from baseline | -0.05 (-0.25) | 2.48 (2.30) | 2.52 (2.40)
Percent change from baseline | 0.2% | 8.9% | 9.1%
Difference from Placebo
Mean (2-sided 95% C.I.) | - | 2.53 [p<0.01] (0.81, 4.25) | 2.57 (0.83, 4.31)
Median | - | 2.55 | 2.65

Table 5: Mean (Median) Change from Baseline for Lean Body Mass, Fat Mass and Body Weight
 | Placebo |  | Half-Dose SEROSTIM [approximately 0.1 mg/kg every other day] |  | Full-Dose SEROSTIM [approximately 0.1 mg/kg daily]
 | N | Mean (Median) | n | Mean (Median) | n | Mean (Median)
Lean body mass (kg) (by BIS) | 222 | 0.97 (0.67) | 223 | 3.89 (3.65) | 205 | 5.84 (5.47)
Fat mass (kg) (by DXA) | 94 | 0.03 (0.01) | 100 | -1.25 (-1.23) | 85 | -1.72 (-1.51)
Body weight (kg) | 247 | 0.69 (0.68) | 257 | 2.18 (2.15) | 253 | 2.79 (2.65)

The mean maximum cycle work output until exhaustion increased after 12 weeks by 2.57 kilojoules (kJ) in the SEROSTIM 0.1 mg/kg daily group (p<0.01) and by 2.53 kJ in the SEROSTIM 0.1 mg/kg every other day group (p<0.01) compared with placebo (Table 4). Cycle work output improved approximately 9% in both active treatment arms and decreased <1% in the placebo group. Lean body mass (LBM) and body weight (BW) increased, and fat mass decreased, in a dose-related fashion after treatment with SEROSTIMand placebo (Table 5). The LBM results obtained by BIS were confirmed with DXA.

Patients' perceptions of the impact of 12 weeks of treatment on their wasting symptoms as assessed by the Bristol-Meyers Anorexia/Cachexia Recovery Instrument improved with both doses of SEROSTIMin Clinical Trial 2.

Extension Phase: All patients (n=646) completing the 12-week placebo-controlled phase of Clinical Trial 2 continued SEROSTIM treatment into an extension phase. Five hundred and forty eight of these patients completed an additional 12 weeks of active treatment. In these patients, changes in cycle ergometry work output, LBM, BW, and fat mass either improved further or were maintained with continued SEROSTIM treatment.

16 HOW SUPPLIED/STORAGE AND HANDLING

16.1 How Supplied

SEROSTIM is available in the following forms:

- SEROSTIM single-use vials containing 5 mg with Sterile Water for Injection, USP. Package of 7 vials. NDC 44087-0005-7
- SEROSTIM single-use vials containing 6 mg with Sterile Water for Injection, USP. Package of 7 vials. NDC 44087-0006-7
- SEROSTIM multiple-use vials containing 4 mg with Bacteriostatic Water for Injection, USP (0.9% Benzyl Alcohol). Package of 7 vials. NDC 44087-0004-7

16.2 Storage and Handling

Before reconstitution: Vials of SEROSTIM and diluent should be stored at room temperature, (15°-30°C/59°-86°F). Expiration dates are stated on product labels.

Single-use vials: After reconstitution with Sterile Water for Injection, USP, the reconstituted solution should be used immediately and any unused portion should be discarded.

Multi-use vials: After reconstitution with Bacteriostatic Water for Injection, USP (0.9% Benzyl Alcohol), the reconstituted solution should be stored under refrigeration (2-8°C/36-46° F) for up to 14 days.

Avoid freezing reconstituted vials of SEROSTIM.

17 PATIENT COUNSELING INFORMATION

Patients being treated with SEROSTIM should be informed of the potential benefits and risks associated with treatment. Patients should be instructed to contact their physician should they experience any side effects or discomfort during treatment with SEROSTIM.

It is recommended that SEROSTIM be administered using sterile, disposable syringes and needles. Patients should be thoroughly instructed in the importance of proper disposal and cautioned against any reuse of needles and syringes. An appropriate container for the disposal of used syringes and needles should be employed.

Patients should be instructed to rotate injection sites to avoid localized tissue atrophy.

Never Share a SEROSTIM Pen or Needle Between Patients

Counsel patients that they should never share SEROSTIM or SEROSTIM injection devices with another person, even if the needle or nozzle is changed. Sharing of SEROSTIM or SEROSTIM injection devices between patients may pose a risk of transmission of infection.

Patients should be informed about the management of common side effects related to tissue turgor, glucose intolerance and musculoskeletal discomfort.

Manufactured for: EMD Serono, Inc., Rockland, MA 02370

PRINCIPAL DISPLAY PANEL - 4 mg Kit Carton

Serostim® 4 mg
(somatropin) for injection

4 mg
For subcutaneous injection
Rx Only

7 vials of SEROSTIM
7 vials of Bacteriostatic Water for Injection, USP (0.9 % Benzyl Alcohol)

NDC 44087-0004-7

EMD Serono

PRINCIPAL DISPLAY PANEL - 5 mg Kit Carton

Serostim® 5 mg
(somatropin) for injection

5 mg
For subcutaneous injection
Rx Only

7 vials SEROSTIM
7 vials Sterile Diluent

NDC 44087-0005-7

EMD Serono

PRINCIPAL DISPLAY PANEL - 6 mg Kit Carton

Serostim® 6 mg
(somatropin) for injection

6 mg
For subcutaneous injection
Rx Only

7 vials SEROSTIM
7 vials Sterile Diluent

NDC 44087-0006-7

EMD Serono